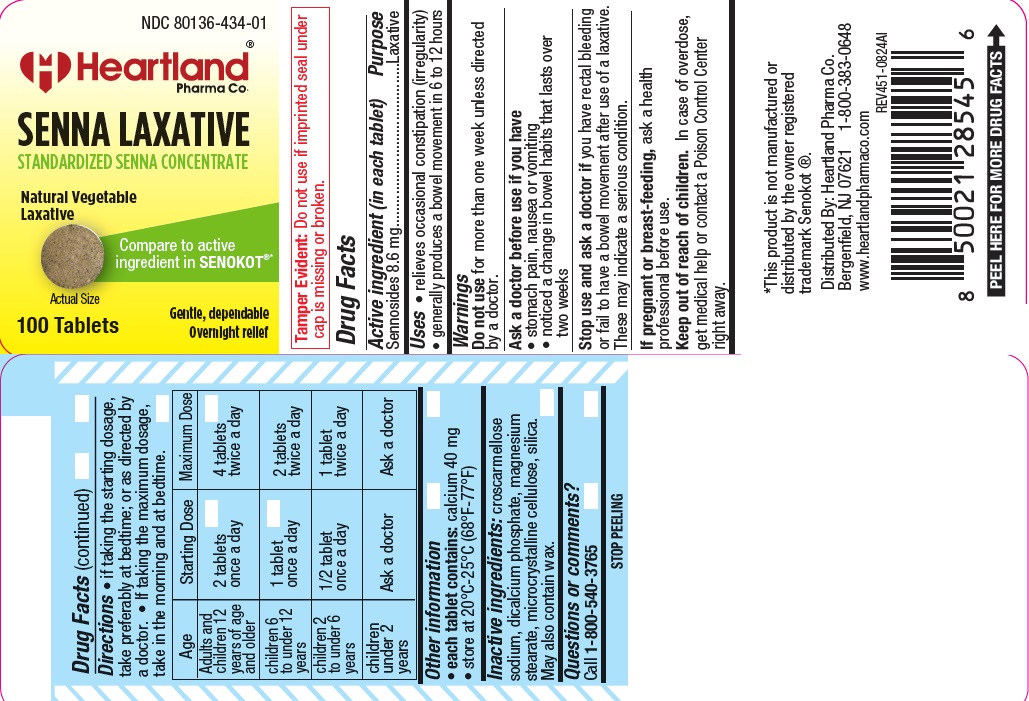 DRUG LABEL: SENNA LAXATIVE
NDC: 80136-434 | Form: TABLET
Manufacturer: Heartland Pharma Co.
Category: otc | Type: HUMAN OTC DRUG LABEL
Date: 20251204

ACTIVE INGREDIENTS: SENNOSIDES 8.6 mg/1 1
INACTIVE INGREDIENTS: CARNAUBA WAX; CELLULOSE, MICROCRYSTALLINE; CROSCARMELLOSE SODIUM; DIBASIC CALCIUM PHOSPHATE DIHYDRATE; MAGNESIUM STEARATE; SILICON DIOXIDE

hpc 451AL 434

Active ingredient (in each tablet)

Sennosides 8.6 mg

Purpose

Laxative

Uses

- relieves occasional constipation (irregularity)

- generally produces bowel movement in 6 to 12 hours

Warnings

Do not use for more than one week unless directed by a doctor.

Ask a doctor before use if you have
• stomach pain, nausea or vomiting
• noticed a change in bowel habits that lasts over two weeks
Stop use and ask a doctor if you have rectal bleeding

or fail to have a bowel movement after use of a laxative.
These may indicate a serious condition.
If pregnant or breast-feeding, ask a health professional before use.

Keep out of reach of children. In case of overdose, get medical help or contact a Poison Control Center right away.

Directions

• if taking the starting dosage,
take preferably at bedtime; or as directed by
a doctor. • If taking the maximum dosage,
take in the morning and at bedtime.

Age | Starting Dose | Maximum Dose
adults and children 12 years of age and older | 2 tablets once a day | 4 tablets twice a day
children 6 to under 12 years | 1 tablets once a day | 2 tablets twice a day
children 2 to under 6 years | 1/2 tablets once a day | 1 tablets twice a day
children to under 2 years | Ask a doctor | Ask a doctor

Other information

- each tablet contains: calcium 40 mg
- store at 20°C-25°C (68°F-77°F)

Inactive ingredients

croscarmellose sodium, dicalcium phosphate, magnesium stearate, microcrystalline cellulose, silica. May also contain wax.